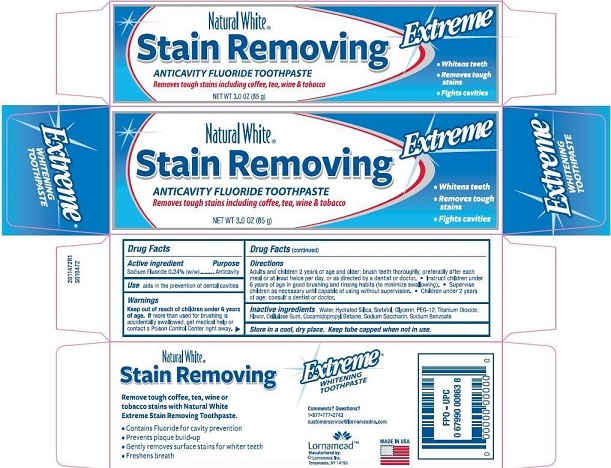 DRUG LABEL: Lornamead
NDC: 62721-0472 | Form: PASTE, DENTIFRICE
Manufacturer: Lornamead
Category: otc | Type: HUMAN OTC DRUG LABEL
Date: 20190218

ACTIVE INGREDIENTS: SODIUM FLUORIDE 0.24 g/100 g
INACTIVE INGREDIENTS: SORBITOL; WATER; SACCHARIN SODIUM; SODIUM BENZOATE; POLYETHYLENE GLYCOL 600; TITANIUM DIOXIDE; GLYCERIN; HYDRATED SILICA; COCAMIDOPROPYL BETAINE; CARBOXYMETHYLCELLULOSE SODIUM, UNSPECIFIED FORM

Lornamead Stain Removing Extreme

Drug Facts

Active ingredient

Sodium fluoride 0.24% (w/w)

Purpose

Anticavity

INDICATIONS AND USAGE

Use aids in the prevention of dental cavities

Warnings

Keep out of reach of children under 6 years of age. If more than used for brushing is accidentally swallowed, get medical help or contact a Poison Control Center right away.

Directions

Adults and children 2 years of age and older: Brush teeth thoroughly, preferably after each meal or at least twice per day or as recommended by a dentist or doctor.

- Instruct children under 6 years of age in good brushing and rinsing habits (to minimize swallowing).
- Supervise children as necessary until capable of using without supervision.
- Children under 2 years of age: consult a dentist or doctor.

INACTIVE INGREDIENT

Inactive ingredients Water, Hydrated Silica, Sorbitol, Glycerin, PEG-12, Titanium Dioxide, Flavor, Cellulose Gum, Cocamidopropyl Betaine, Sodium Saccharin. Sodium Benzoate

STORAGE AND HANDLING

Store in a cool dry place. Keep tube capped when not in use.

Comments? Questions?

1-877-777-2743

customer service@lornamead.com

Lornamead™

Manufactured by:

Lornamead, Inc.

Tonawanda, NY 14150

MADE IN USA

PACKAGE LABEL

Natural White

Stain Removing Extreme

ANTICAVITY FLUORIDE TOOTHPASTE

Removes tough stains including coffee, tea, wine & tobacco

NET WT 3.0 OZ (85 g)